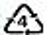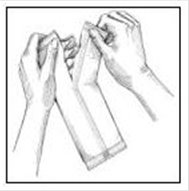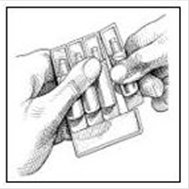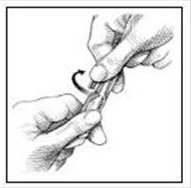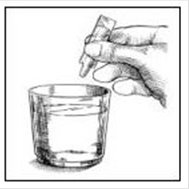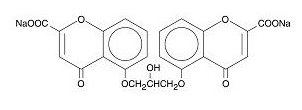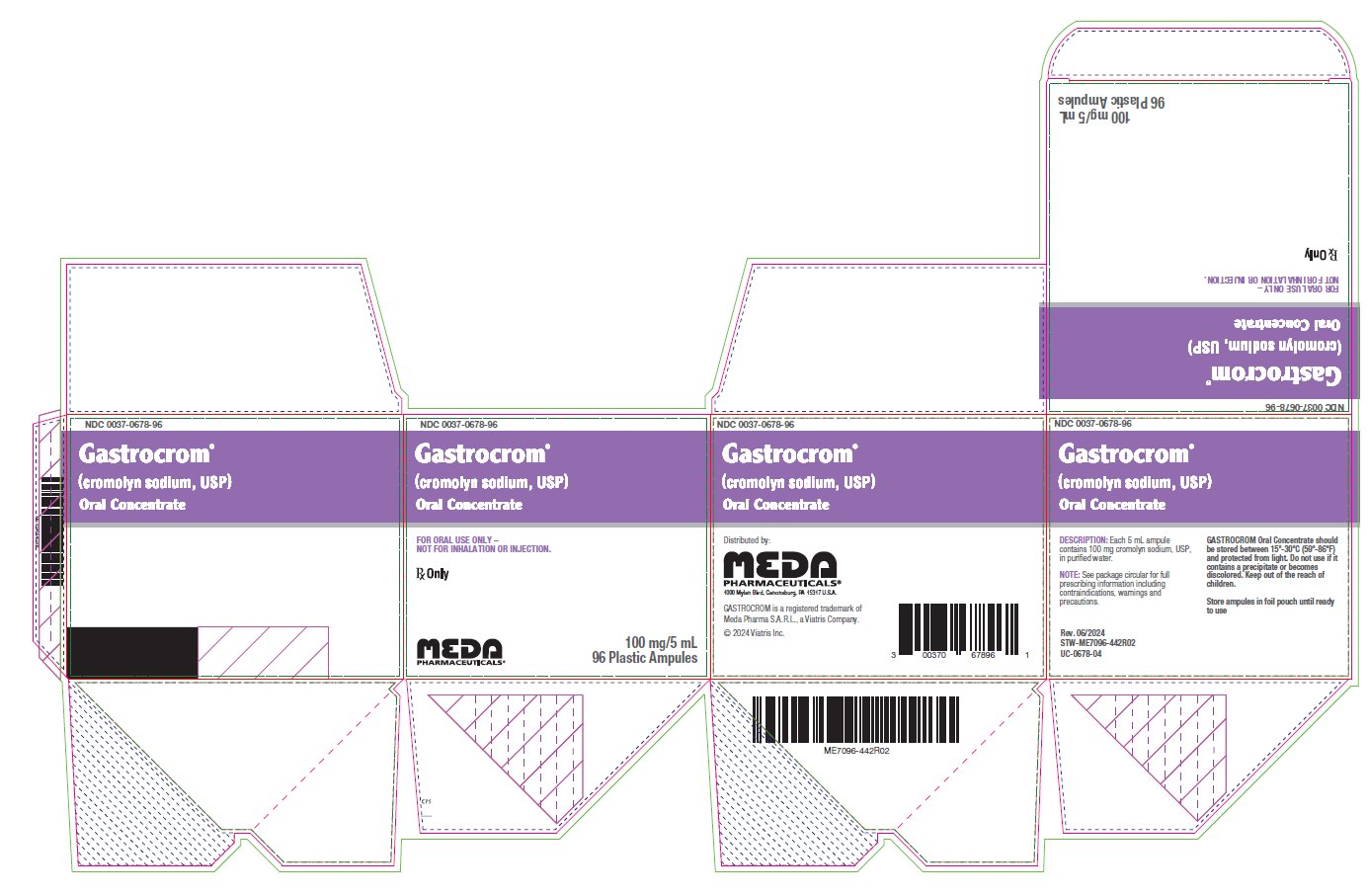 DRUG LABEL: Gastrocrom
NDC: 0037-0678 | Form: LIQUID
Manufacturer: Viatris Specialty LLC
Category: prescription | Type: HUMAN PRESCRIPTION DRUG LABEL
Date: 20240626

ACTIVE INGREDIENTS: CROMOLYN SODIUM 20 mg/1 mL
INACTIVE INGREDIENTS: WATER

Gastrocrom (cromolyn sodium, USP) Oral Concentrate
For Oral Use Only – Not for Inhalation or Injection.

DESCRIPTION

Each 5 mL ampule of GASTROCROM contains 100 mg cromolyn sodium, USP, in purified water. Cromolyn sodium is a hygroscopic, white powder having little odor. It may leave a slightly bitter aftertaste. GASTROCROM (cromolyn sodium, USP) Oral Concentrate is clear, colorless, and sterile. It is intended for oral use.

Chemically, cromolyn sodium is disodium 5,5’-[(2-hydroxytrimethylene)dioxy]bis[4-oxo-4H-1-benzopyran-2-carboxylate]. The empirical formula is C23H14Na2O11; the molecular weight is 512.34. Its chemical structure is:

Pharmacologic Category: Mast cell stabilizer

Therapeutic Category: Antiallergic

CLINICAL PHARMACOLOGY

In vitro and in vivo animal studies have shown that cromolyn sodium inhibits the release of mediators from sensitized mast cells. Cromolyn sodium acts by inhibiting the release of histamine and leukotrienes (SRS-A) from the mast cell.

Cromolyn sodium has no intrinsic vasoconstrictor, antihistamine, or glucocorticoid activity.

Cromolyn sodium is poorly absorbed from the gastrointestinal tract. No more than 1% of an administered dose is absorbed by humans after oral administration, the remainder being excreted in the feces. Very little absorption of cromolyn sodium was seen after oral administration of 500 mg by mouth to each of 12 volunteers. From 0.28 to 0.50% of the administered dose was recovered in the first 24 hours of urinary excretion in 3 subjects. The mean urinary excretion of an administered dose over 24 hours in the remaining 9 subjects was 0.45%.

CLINICAL STUDIES

Four randomized, controlled clinical trials were conducted with GASTROCROM in patients with either cutaneous or systemic mastocytosis; two of which utilized a placebo-controlled crossover design, one utilized an active-controlled (chlorpheniramine plus cimetidine) crossover design, and one utilized a placebo-controlled parallel group design. Due to the rare nature of this disease, only 36 patients qualified for study entry, of whom 32 were considered evaluable. Consequently, formal statistical analyses were not performed. Clinically significant improvement in gastrointestinal symptoms (diarrhea, abdominal pain) were seen in the majority of patients with some improvement also seen for cutaneous manifestations (urticaria, pruritus, flushing) and cognitive function.

The benefit seen with GASTROCROM 200 mg QID was similar to chlorpheniramine (4 mg QID) plus cimetidine (300 mg QID) for both cutaneous and systemic symptoms of mastocytosis.

Clinical improvement occurred within 2-6 weeks of treatment initiation and persisted for 2-3 weeks after treatment withdrawal. GASTROCROM did not affect urinary histamine levels or peripheral eosinophilia, although neither of these variables appeared to correlate with disease severity. Positive clinical benefits were also reported for 37 of 51 patients who received GASTROCROM in United States and foreign humanitarian programs.

INDICATIONS AND USAGE

GASTROCROM is indicated in the management of patients with mastocytosis. Use of this product has been associated with improvement in diarrhea, flushing, headaches, vomiting, urticaria, abdominal pain, nausea, and itching in some patients.

CONTRAINDICATIONS

GASTROCROM is contraindicated in those patients who have shown hypersensitivity to cromolyn sodium.

WARNINGS

The recommended dosage should be decreased in patients with decreased renal or hepatic function. Severe anaphylactic reactions may occur rarely in association with cromolyn sodium administration.

PRECAUTIONS

In view of the biliary and renal routes of excretion of GASTROCROM, consideration should be given to decreasing the dosage of the drug in patients with impaired renal or hepatic function.

Carcinogenesis, Mutagenesis, and Impairment of Fertility

In carcinogenicity studies in mice, hamsters, and rats, cromolyn sodium had no neoplastic effects at intraperitoneal doses up to 150 mg/kg three days per week for 12 months in mice, at intraperitoneal doses up to 53 mg/kg three days per week for 15 weeks followed by 17.5 mg/kg three days per week for 37 weeks in hamsters, and at subcutaneous doses up to 75 mg/kg six days per week for 18 months in rats. These doses in mice, hamsters, and rats are less than the maximum recommended daily oral dose in adults and children on a mg/m^2 basis.

Cromolyn sodium showed no mutagenic potential in Ames Salmonella/microsome plate assays, mitotic gene conversion in Saccharomyces cerevisiae and in an in vitro cytogenetic study in human peripheral lymphocytes.

In rats, cromolyn sodium showed no evidence of impaired fertility at subcutaneous doses up to 175 mg/kg in males (approximately equal to the maximum recommended daily oral dose in adults on a mg/m^2 basis) and 100 mg/kg in females (less than the maximum recommended daily oral dose in adults on a mg/m^2 basis).

Pregnancy

In reproductive studies in pregnant mice, rats, and rabbits, cromolyn sodium produced no evidence of fetal malformations at subcutaneous doses up to 540 mg/kg in mice (approximately equal to the maximum recommended daily oral dose in adults on a mg/m^2 basis) and 164 mg/kg in rats (less than the maximum recommended daily oral dose in adults on a mg/m^2 basis) or at intravenous doses up to 485 mg/kg in rabbits (approximately 4 times the maximum recommended daily oral dose in adults on a mg/m^2 basis). There are, however, no adequate and well controlled studies in pregnant women.

Because animal reproduction studies are not always predictive of human response, this drug should be used during pregnancy only if clearly needed.

Drug Interaction During Pregnancy

In pregnant mice, cromolyn sodium alone did not cause significant increases in resorptions or major malformations at subcutaneous doses up to 540 mg/kg (approximately equal to the maximum recommended daily oral dose in adults on a mg/m^2 basis). Isoproterenol alone increased both resorptions and major malformations (primarily cleft palate) at a subcutaneous dose of 2.7 mg/kg (approximately 7 times the maximum recommended daily inhalation dose in adults on a mg/m^2 basis). The incidence of major malformations increased further when cromolyn sodium at a subcutaneous dose of 540 mg/kg was added to isoproterenol at a subcutaneous dose of 2.7 mg/kg. No such interaction was observed in rats or rabbits.

Nursing Mothers

It is not known whether this drug is excreted in human milk. Because many drugs are excreted in human milk, caution should be exercised when GASTROCROM is administered to a nursing woman.

Pediatric Use

In adult rats no adverse effects of cromolyn sodium were observed at oral doses up to 6144 mg/kg (approximately 25 times the maximum recommended daily oral dose in adults on a mg/m^2 basis). In neonatal rats, cromolyn sodium increased mortality at oral doses of 1000 mg/kg or greater (approximately 9 times the maximum recommended daily oral dose in infants on a mg/m^2 basis) but not at doses of 300 mg/kg or less (approximately 3 times the maximum recommended daily oral dose in infants on a mg/m^2 basis). Plasma and kidney concentrations of cromolyn after oral administration to neonatal rats were up to 20 times greater than those in older rats. In term infants up to six months of age, available clinical data suggest that the dose should not exceed 20 mg/kg/day. The use of this product in pediatric patients less than two years of age should be reserved for patients with severe disease in which the potential benefits clearly outweigh the risks.

Geriatric Use

Clinical studies of GASTROCROM did not include sufficient numbers of subjects aged 65 and over to determine whether they respond differently from younger subjects. Other reported clinical experience has not identified differences in responses between the elderly and younger patients. In general, dose selection for an elderly patient should be cautious, usually starting at the low end of the dosing range, reflecting the greater frequency of decreased hepatic, renal, or cardiac function, and of concomitant disease or other drug therapy.

ADVERSE REACTIONS

Most of the adverse events reported in mastocytosis patients have been transient and could represent symptoms of the disease. The most frequently reported adverse events in mastocytosis patients who have received GASTROCROM during clinical studies were headache and diarrhea, each of which occurred in 4 of the 87 patients. Pruritus, nausea, and myalgia were each reported in 3 patients and abdominal pain, rash, and irritability in 2 patients each. One report of malaise was also recorded.

To report SUSPECTED ADVERSE REACTIONS, contact Meda Pharmaceuticals Inc. at 1-877-999-8406 or FDA at 1-800-FDA-1088 or www.fda.gov/medwatch.

Other Adverse Events: Additional adverse events have been reported during studies in other clinical conditions and from worldwide postmarketing experience. In most cases the available information is incomplete and attribution to the drug cannot be determined. The majority of these reports involve the gastrointestinal system and include: diarrhea, nausea, abdominal pain, constipation, dyspepsia, flatulence, glossitis, stomatitis, vomiting, dysphagia, esophagospasm.

Other less commonly reported events (the majority representing only a single report) include the following:

Skin: pruritus, rash, urticaria/angioedema, erythema/ burning, photosensitivity

Musculoskeletal: arthralgia, myalgia, stiffness/weakness of legs

Neurologic: headache, dizziness, hypoesthesia, paresthesia, migraine, convulsions, flushing

Psychiatric: psychosis, anxiety, depression, hallucinations, behavior change, insomnia, nervousness

Heart Rate: tachycardia, premature ventricular contractions (PVCs), palpitations

Respiratory: pharyngitis, dyspnea

Miscellaneous: fatigue, edema, unpleasant taste, chest pain, postprandial lightheadedness and lethargy, dysuria, urinary frequency, purpura, hepatic function test abnormal, polycythemia, neutropenia, pancytopenia, tinnitus, lupus erythematosus (LE) syndrome

DOSAGE AND ADMINISTRATION

NOT FOR INHALATION OR INJECTION. SEE DIRECTIONS FOR USE.

The usual starting dose is as follows:

Adults and Adolescents (13 Years and Older)

Two ampules four times daily, taken one-half hour before meals and at bedtime.

Children 2-12 Years

One ampule four times daily, taken one-half hour before meals and at bedtime.

Pediatric Patients Under 2 Years

Not recommended.

If satisfactory control of symptoms is not achieved within two to three weeks, the dosage may be increased but should not exceed 40 mg/kg/day.

Patients should be advised that the effect of GASTROCROM therapy is dependent upon its administration at regular intervals, as directed.

Maintenance Dose

Once a therapeutic response has been achieved, the dose may be reduced to the minimum required to maintain the patient with a lower degree of symptomatology. To prevent relapses, the dosage should be maintained.

Administration

GASTROCROM should be administered as a solution at least 1/2 hour before meals and at bedtime after preparation according to the following directions:

1. Break open ampule(s) and squeeze liquid contents of ampule(s) into a glass of water.
2. Stir solution.
3. Drink all of the liquid.

HOW SUPPLIED

GASTROCROM Oral Concentrate is an unpreserved, colorless solution supplied in a low density polyethylene plastic unit dose ampule with 8 ampules per foil pouch. Each 5 mL ampule contains 100 mg cromolyn sodium, USP, in purified water.

NDC 0037-0678-08 8 ampules x 5 mL

NDC 0037-0678-96 96 ampules x 5 mL

GASTROCROM Oral Concentrate should be stored between 15°-30°C (59°-86°F) and protected from light. Do not use if it contains a precipitate or becomes discolored. Keep out of the reach of children.

Store ampules in foil pouch until ready for use.

Distributed by:
Meda Pharmaceuticals®
1000 Mylan Blvd
Canonsburg, PA 15317 U.S.A.
GASTROCROM is a registered trademark of Meda Pharma S.A.R.L., a Viatris Company.
© 2024 Viatris Inc.

Rev. 06/2024
STW-ME7096-642R02
IN-0678-03

PATIENT INSTRUCTIONS

Gastrocrom®
(cromolyn sodium, USP)
Oral Concentrate

For Oral Use Only – Not for Inhalation or Injection.

How to Use GASTROCROM:
As with all prescription drugs, follow the directions for dosage that your physician recommends.

The effect of GASTROCROM therapy is dependent upon its administration at REGULAR intervals, for as long as recommended by your physician.

Usual Starting Dose:
Adults and Adolescents (13 Years and Older):
Two ampules four times daily, taken one-half hour before meals and at bedtime.

Children 2-12 Years:
One ampule four times daily, taken one-half hour before meals and at bedtime.

Note:
Your physician may decide to increase OR decrease your dosage to achieve optimum results with GASTROCROM. However, do not change your dose or stop taking GASTROCROM without first consulting your physician.

Care & Storage:
GASTROCROM Oral Concentrate should be stored between 15°-30°C (59°-86°F) and protected from light. Do not use if it contains a precipitate (particles or cloudiness) or becomes discolored. Keep out of the reach of children.

Store ampules in foil pouch until ready for use.

Recycling Information: GASTROCROM Oral Concentrate ampules are made with a low density polyethylene plastic (recycling material code: LDPE).

Directions for Use:

1.Open foil pouch by tearing at serrated edge as shown.

2.Remove ampule(s) from the strip.

3.Open the ampule by twisting off the tabbed top section.

4.Squeeze liquid contents into a glass of water. Stir solution. Drink all of the liquid. Discard the empty ampule.

Distributed by:
Meda Pharmaceuticals®
1000 Mylan Blvd
Canonsburg, PA 15317 U.S.A.
GASTROCROM is a registerd trademark of Meda Pharma S.A.R.L., a Viatris Company.
© 2024 Viatris Inc.

Rev. 06/2024
STW-ME7096-642R02
IN-0678-03

PRINCIPAL DISPLAY PANEL – 100 mg/5 mL

NDC 0037-0678-96

Gastrocrom ®
(cromolyn sodium, USP)
Oral Concentrate

FOR ORAL USE ONLY –
NOT FOR INHALATION OR INJECTION.

Rx Only

100 mg/5 mL
96 Plastic Ampules

DESCRIPTION: Each 5 mL ampule
contains 100 mg cromolyn sodium, USP,
in purified water.

NOTE: See package circular for full
prescribing information including
contraindications, warnings and
precautions.

GASTROCROM Oral Concentrate should
be stored between 15º-30ºC (59º-86ºF)
and protected from light. Do not use if it
contains a precipitate or becomes
discolored. Keep out of the reach of
children.

Store ampules in foil pouch until ready
to use

Rev. 06/2024
STW-ME7096-442R02
UC-0678-04

Distributed by:
MEDA
PHARMACEUTICALS®
1000 Mylan Blvd, Canonsburg, PA 15317 U.S.A.

GASTROCROM is a registered trademark of
Meda Pharma S.A.R.L., a Viatris Company.

© 2024 Viatris Inc.